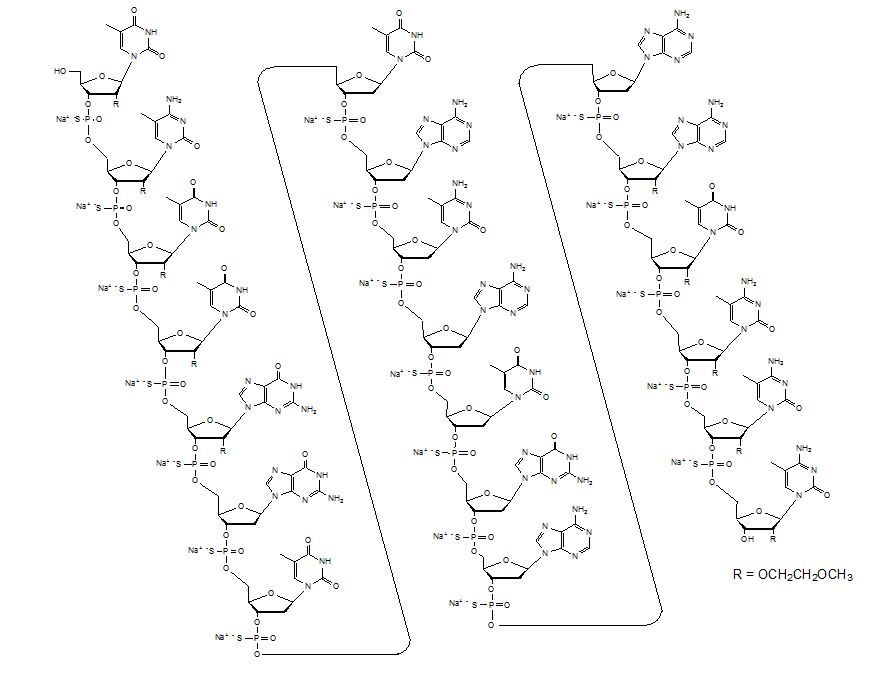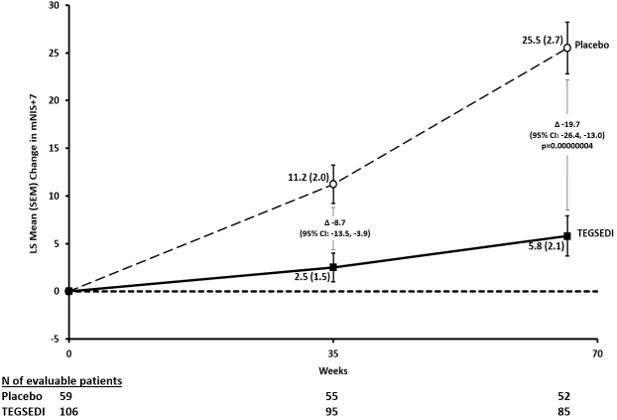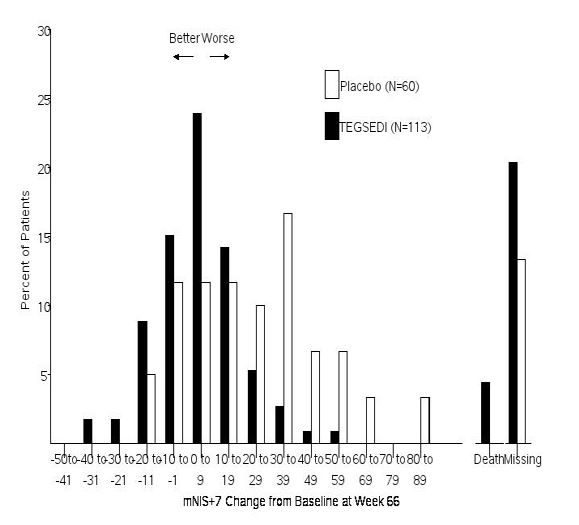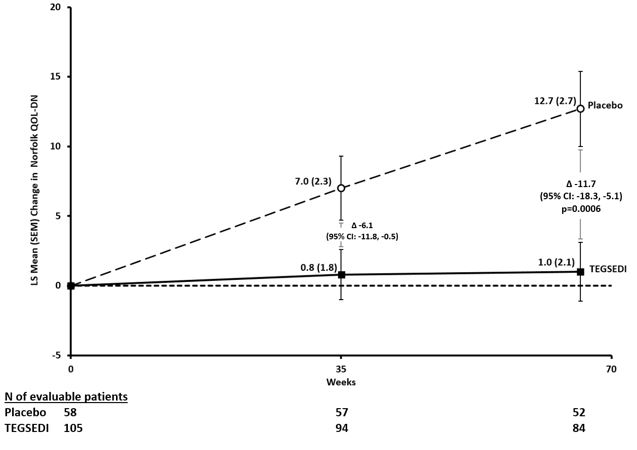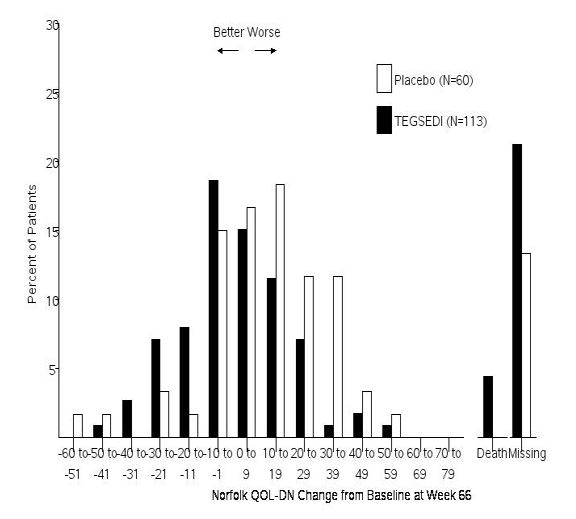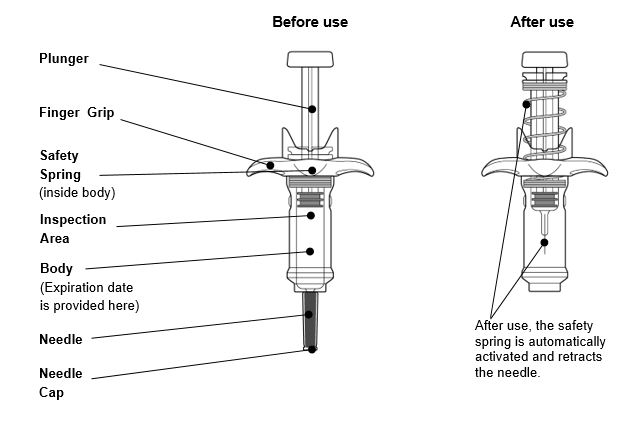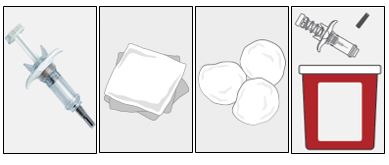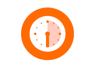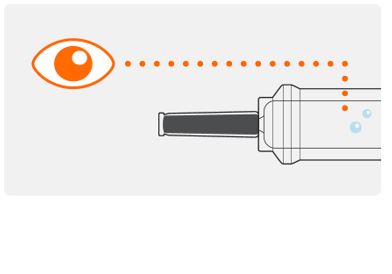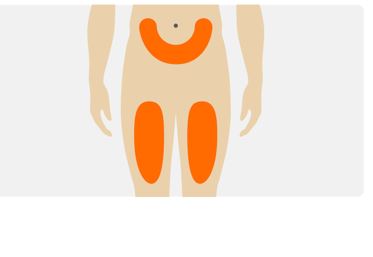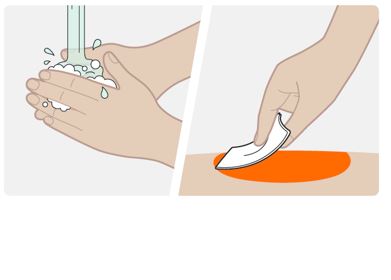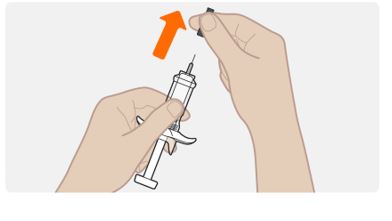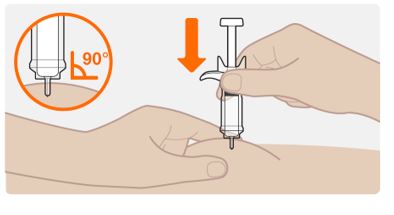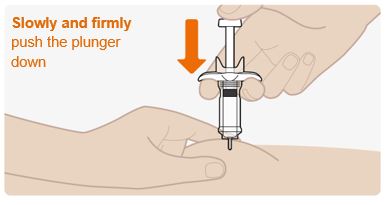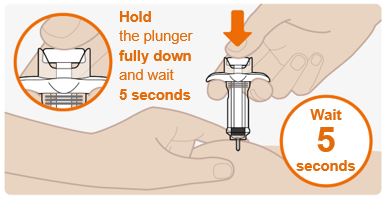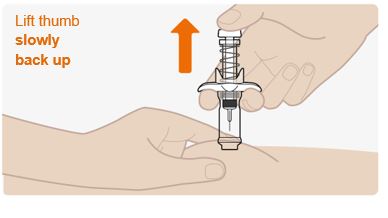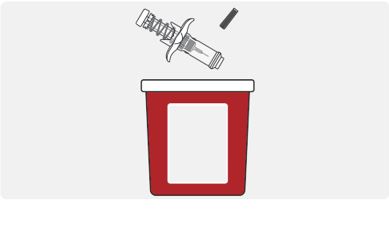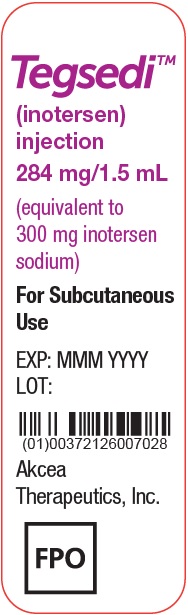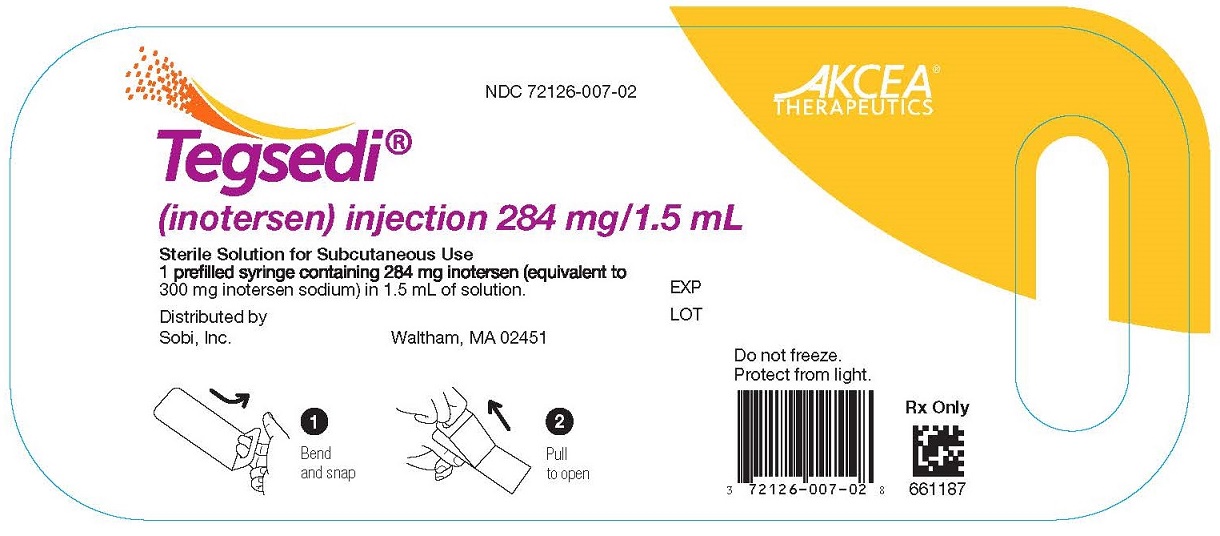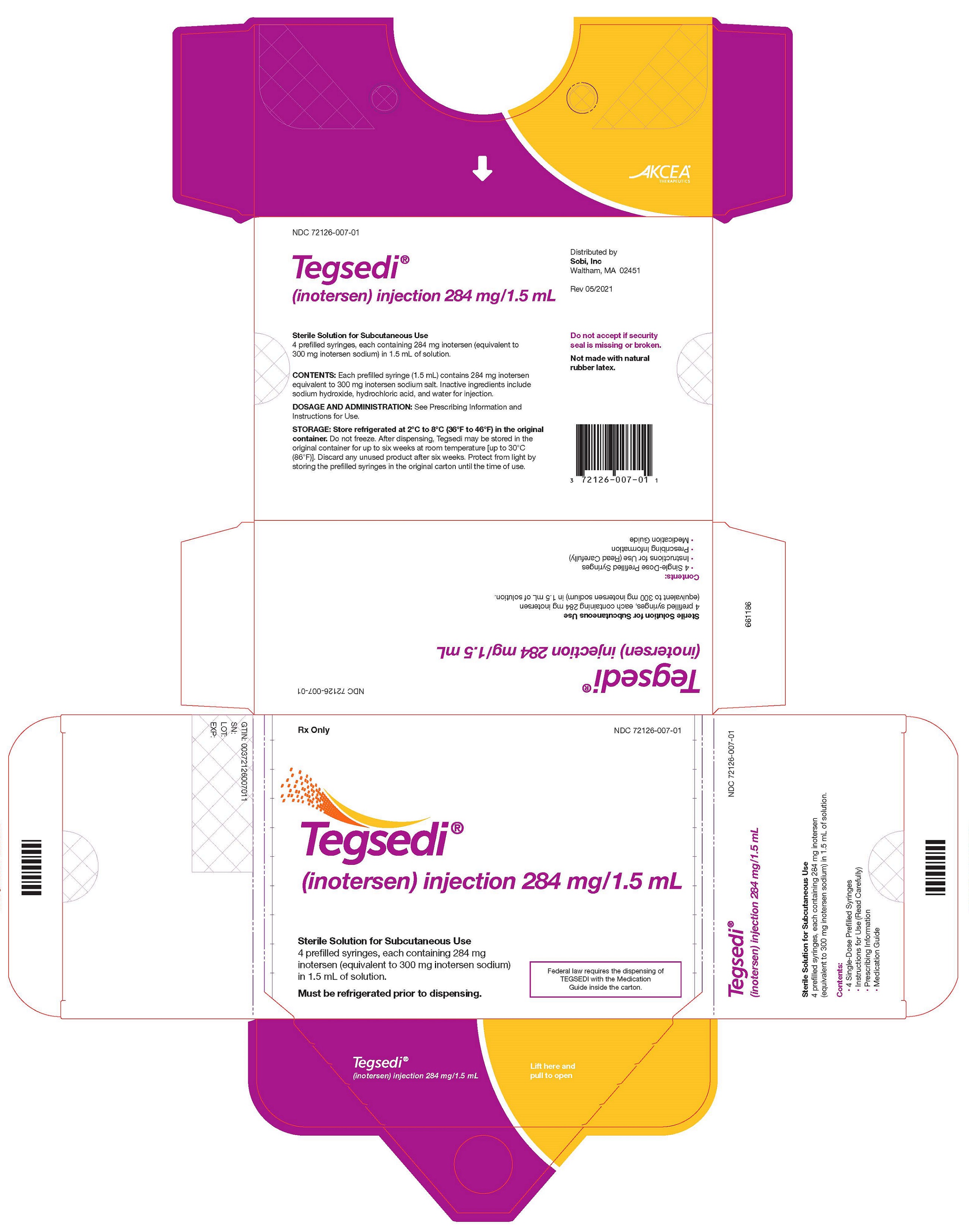 DRUG LABEL: Tegsedi
NDC: 72126-007 | Form: INJECTION, SOLUTION
Manufacturer: Akcea Therapeutics, Inc.
Category: prescription | Type: HUMAN PRESCRIPTION DRUG LABEL
Date: 20240125

ACTIVE INGREDIENTS: INOTERSEN SODIUM 284 mg/1.5 mL
INACTIVE INGREDIENTS: HYDROCHLORIC ACID; SODIUM HYDROXIDE; WATER

HIGHLIGHTS OF PRESCRIBING INFORMATION

These highlights do not include all the information needed to use TEGSEDI® safely and effectively. See full prescribing information for TEGSEDI.
TEGSEDI (inotersen) injection, for subcutaneous use
Initial U.S. Approval: 2018

RECENT MAJOR CHANGES

Dosage and Administration (2.4) | 1/2024
Warnings and Precautions (5.1, 5.6) | 1/2024

WARNING: THROMBOCYTOPENIA AND GLOMERULONEPHRITIS

See full prescribing information for complete boxed warning.

Thrombocytopenia

- TEGSEDI causes reductions in platelet count that may result in sudden and unpredictable thrombocytopenia, which can be life-threatening. (5.1)
- Testing prior to treatment and monitoring during treatment is required (2.3, 2.4, 5.1)

Glomerulonephritis

- TEGSEDI can cause glomerulonephritis that may require immunosuppressive treatment and may result in dialysis-dependent renal failure. (5.2)
- Testing prior to treatment and monitoring during treatment is required (2.3, 2.4, 5.2)

TEGSEDI is available only through a restricted distribution program called the TEGSEDI REMS Program (5.3).

1 INDICATIONS AND USAGE

TEGSEDI is a transthyretin-directed antisense oligonucleotide indicated for treatment of the polyneuropathy of hereditary transthyretin-mediated amyloidosis in adults (1).

2 DOSAGE AND ADMINISTRATION

- The recommended dosage is 284 mg administered by subcutaneous injection once weekly. (2.1)
- Laboratory tests must be measured prior to treatment, continue to be monitored after treatment initiation, and for 8 weeks following discontinuation of treatment, as directed. (2.3, 2.4)

3 DOSAGE FORMS AND STRENGTHS

Injection: 284 mg/ 1.5 mL in a single-dose prefilled syringe (3)

4 CONTRAINDICATIONS

- Platelet count less than 100 x 10^9/L (4, 5.1)
- History of acute glomerulonephritis caused by TEGSEDI (4, 5.2)
- Patients with a history of a hypersensitivity reaction to TEGSEDI (4, 5.7)

5 WARNINGS AND PRECAUTIONS

- Stroke and Cervicocephalic Arterial Dissection: These adverse events occurred within 2 days of first dose and with symptoms of cytokine release. Educate patients on symptoms of stroke and central nervous system arterial dissection. (5.4)
- Inflammatory and Immune Effects: Serious neurologic adverse reactions consistent with inflammatory and immune effects occurred. (5.5)
- Liver Injury: Monitor alanine amino-transferase, aspartate aminotransferase, and total bilirubin every 4 months during treatment and in case of symptoms of hepatic dysfunction. (5.6)
- Hypersensitivity Reactions: If these occur, discontinue and initiate appropriate therapy. (5.7)
- Uninterpretable Platelet Counts: Reaction between Antiplatelet Antibodies and ethylenediaminetetra-acetic acid: Platelet clumping can cause uninterpretable platelet measurement; repeat test if this is suspected. (5.8)
- Reduced Serum Vitamin A Levels and Recommended Supplementation: Supplement with the recommended daily allowance of vitamin A. Refer to an ophthalmologist if ocular symptoms suggestive of vitamin A deficiency occur. (5.9)

6 ADVERSE REACTIONS

The most common adverse reactions (those that occurred in at least 20% of TEGSEDI-treated patients and more frequently than on placebo) were injection site reactions, nausea, headache, fatigue, thrombocytopenia, and fever (6.1).

To report SUSPECTED ADVERSE REACTIONS, contact Sobi, Inc. at 1-833-642-5232 or FDA at 1-800-FDA-1088 or www.fda.gov/medwatch.

FULL PRESCRIBING INFORMATION

WARNING: THROMBOCYTOPENIA AND GLOMERULONEPHRITIS

Thrombocytopenia

TEGSEDI causes reductions in platelet count that may result in sudden and unpredictable thrombocytopenia, which can be life-threatening. One clinical trial patient died from intracranial hemorrhage.

TEGSEDI is contraindicated in patients with a platelet count below 100 x 10^9/L [see Contraindications (4) and Warnings and Precautions (5.2)].

Prior to starting TEGSEDI, obtain a platelet count [see Dosage and Administration (2.3)]. During treatment, monitor platelet counts weekly if values are 75 x 10^9/L or greater, and more frequently if values are less than 75 x 10^9/L [see Dosage and Administration (2.4) and Warnings and Precautions (5.1)].

If a patient develops signs or symptoms of thrombocytopenia, obtain a platelet count as soon as possible. The patient should not receive additional TEGSEDI unless a platelet count is determined to be interpretable and acceptable by a medical professional [see Warnings and Precautions (5.1)].

Following discontinuation of treatment for any reason, continue to monitor platelet count for 8 weeks, or longer if platelet counts are less than 100 x 10^9/L, to verify that platelet counts remain above 75 x 10^9/L [see Dosage and Administration (2.4)].

Glomerulonephritis

TEGSEDI can cause glomerulonephritis that may require immunosuppressive treatment and may result in dialysis-dependent renal failure. One clinical trial patient who developed glomerulonephritis and did not receive immunosuppressive treatment remained dialysis-dependent. In clinical trials, cases of glomerulonephritis were accompanied by nephrotic syndrome, which can have manifestations of edema, hypercoagulability with venous or arterial thrombosis, and increased susceptibility to infection [see Warnings and Precautions (5.2)].

TEGSEDI should generally not be initiated in patients with urinary protein to creatinine ratio (UPCR) of 1000 mg/g or higher [see Dosage and Administration (2.4) and Warnings and Precautions (5.2)].

Prior to starting TEGSEDI, measure the serum creatinine, estimated glomerular filtration rate (eGFR), urine protein to creatinine ratio (UPCR), and perform a urinalysis [see Dosage and Administration (2.3)]. During treatment, monitor serum creatinine, eGFR urinalysis, and UPCR every two weeks. TEGSEDI should not be given to patients who develop a UPCR of 1000 mg/g or higher, or eGFR below 45 mL/minute/1.73 m^2, pending further evaluation of the cause.

If a dose is held, once eGFR increases to ≥45 mL/minute/1.73 m^2, UPCR decreases to below 1000 mg/g, or the underlying cause of the decline in renal function is corrected, weekly dosing may be reinitiated. In patients with UPCR of 2000 mg/g or higher, perform further evaluation for acute glomerulonephritis, as clinically indicated. If acute glomerulonephritis is confirmed, TEGSEDI should be permanently discontinued [see Dosage and Administration (2.4) and Warnings and Precautions (5.2)].

TEGSEDI REMS Program

Because of the risks of serious bleeding caused by severe thrombocytopenia and because of glomerulonephritis, both of which require frequent monitoring, TEGSEDI is available only through a restricted distribution program under a Risk Evaluation and Mitigation Strategy (REMS) called the TEGSEDI REMS Program [see Warnings and Precautions (5.3)].

1 INDICATIONS AND USAGE

TEGSEDI is indicated for the treatment of the polyneuropathy of hereditary transthyretin-mediated amyloidosis in adults.

2 DOSAGE AND ADMINISTRATION

2.1 Dosing Information

The recommended dose of TEGSEDI is 284 mg injected subcutaneously once weekly.

For consistency of dosing, patients should be instructed to give the injection on the same day every week.

If a dose is missed, patients should be instructed to take the missed dose as soon as possible, unless the next scheduled dose is within 2 days. In this situation, the patient should be directed to skip the missed dose and take the next scheduled dose on the scheduled day.

2.2 Administration

- TEGSEDI is intended for subcutaneous use only.
- The first injection administered by the patient or caregiver should be performed under the guidance of an appropriately qualified healthcare professional. Patients and/or caregivers should be trained in the subcutaneous administration of TEGSEDI in accordance with the Instructions for Use.
- Parenteral drug products should be inspected visually for particulate matter and discoloration prior to administration, whenever solution and container permit [see How Supplied/Storage and Handling (16)].
- Sites for injection include the abdomen, upper thigh region, or outer area of the upper arm. It is important to rotate sites for injection.
  - If injected in the upper arm, the injection should be administered by a person other than the patient.
  - Injection should be avoided at the waistline and other sites where pressure or rubbing from clothing may occur.
  - TEGSEDI should not be injected into areas of skin disease or injury.
  - Tattoos and scars should also be avoided.
- TEGSEDI prefilled syringe should be allowed to reach room temperature prior to injection.
  - Remove from refrigerated storage at least 30 minutes prior to use.
  - Other warming methods should not be used.
- Use each prefilled syringe only once.

2.3 Assessment Prior to Initiating TEGSEDI

Measure platelet count, serum creatinine, estimated glomerular filtration rate (eGFR), urine protein to creatinine ratio (UPCR), alanine aminotransferase (ALT), aspartate aminotransferase (AST), and total bilirubin, and perform urinalysis prior to treatment with TEGSEDI and as directed following treatment initiation [see Dosage and Administration (2.4) and Warnings and Precautions (5.1 and 5.2)].

2.4 Laboratory Testing and Monitoring to Assess Safety after Initiating TEGSEDI

Monitor platelet count, serum creatinine, estimated glomerular filtration rate (eGFR), urinalysis, urine protein to creatinine ratio (UPCR), alanine aminotransferase (ALT), aspartate aminotransferase (AST), and total bilirubin during treatment with TEGSEDI, and for 8 weeks following discontinuation of treatment.

Platelet Count

Do not initiate TEGSEDI in patients with a platelet count less than 100 x 10^9/L. Monitor platelet count during the entire course of treatment with Tegsedi and for 8 weeks following discontinuation of treatment. Recommendations for platelet monitoring frequency and TEGSEDI dosing are specified in Table 1. If a patient develops signs or symptoms of thrombocytopenia, obtain a platelet count as soon as possible, and hold dosing until platelet count is confirmed. Recheck the platelet count as soon as possible if a platelet measurement is uninterpretable (e.g., clumped sample) [see Warnings and Precautions (5.8].

Table 1: TEGSEDI Monitoring and Treatment Recommendations for Platelet Count
Platelet count (x10^9/L) | Monitoring Frequency | Dosing
At least 100 | Weekly | Continue to dose weekly.
At least 75 to less than 100 | Weekly | Stop treatment. Do not restart unless platelet count is greater than 100.
At least 50 to less than 75 | Twice weekly until 3 successive values above 75; then weekly monitoring. | Stop treatment. Do not restart TEGSEDI in patients with thrombocytopenia, unless there have been 3 successive values above 100 and the benefit of TEGSEDI outweighs the risk of thrombocytopenia and potential bleeding.
At least 25 to less than 50* | Twice weekly until 3 successive values above 75; then weekly monitoring.; Consider more frequent monitoring if additional risk factors for bleeding are present.# | Stop treatment. Do not restart TEGSEDI in patients with thrombocytopenia, unless there have been 3 successive values above 100 and the benefit of TEGSEDI outweighs the risk of thrombocytopenia and potential bleeding.; Corticosteroids recommended.; Consider discontinuation of any antiplatelet agents or anticoagulants.
Less than 25*† | Daily until 2 successive values above 25. Then monitor twice weekly until 3 successive values above 75. Then weekly monitoring until stable. | Stop TEGSEDI.; Corticosteroids recommended.; Consider discontinuation of any antiplatelet agents or anticoagulants.
* It is strongly recommended that, unless the patient has a medical contraindication to receiving glucocorticoids, the patient receive glucocorticoid therapy to reverse the platelet decline [see Warnings and Precautions (5.1)].
# Additional risk factors for bleeding include age >60 years, receiving anticoagulant or antiplatelet medicinal products, or prior history of major bleeding events.
†Patients who discontinue therapy with TEGSEDI because of platelet counts below 25 x10^9/L should not reinitiate therapy.

Renal Monitoring

TEGSEDI should generally not be initiated in patients with a urine protein to creatinine ratio (UPCR) of 1000 mg/g or higher. Monitor serum creatinine, estimated glomerular filtration rate (eGFR), urinalysis, and UPCR every 2 weeks during treatment with TEGSEDI. Hold TEGSEDI in patients who develop a UPCR of 1000 mg/g or higher, or estimated glomerular filtration rate (eGFR) below 45 mL/minute/1.73 m^2, pending further evaluation of the cause.

If a dose is held, once eGFR increases to ≥45 mL/minute/1.73 m^2, UPCR decreases to below 1000 mg/g, or the underlying cause of the decline in renal function is corrected, weekly dosing may be reinitiated. In the case of UPCR of 2000 mg/g or higher, perform further evaluation for acute glomerulonephritis, as clinically indicated. If acute glomerulonephritis is confirmed, TEGSEDI should be permanently discontinued.

Liver Tests

Monitor alanine aminotransferase (ALT), aspartate aminotransferase (AST), and total bilirubin monthly during treatment with TEGSEDI; monitor monthly for patients who have received a liver transplant [see Warnings and Precautions (5.6)]. TEGSEDI should be discontinued in patients suspected of developing liver injury induced by TEGSEDI [see Warnings and Precautions (5.6)].

3 DOSAGE FORMS AND STRENGTHS

Injection: 284 mg/1.5 mL clear, colorless to pale yellow solution in a single-dose prefilled syringe.

4 CONTRAINDICATIONS

TEGSEDI is contraindicated in patients with:

- Platelet count below 100 x 10^9/L [see Warnings and Precautions (5.1)]
- History of acute glomerulonephritis caused by TEGSEDI [see Warnings and Precautions (5.2)]
- History of a hypersensitivity reaction to TEGSEDI [see Warnings and Precautions (5.7)].

5 WARNINGS AND PRECAUTIONS

5.1 Thrombocytopenia

TEGSEDI causes reductions in platelet count at any time during treatment that may result in sudden and unpredictable thrombocytopenia that can be life-threatening. In Study 1 [see Clinical studies (14)] , platelet counts below 100 x 10^9/L occurred in 25% of TEGSEDI-treated patients, compared with 2% of patients on placebo. Platelet counts below 75 x 10^9/L occurred in 14% of TEGSEDI-treated patients, compared to no patient on placebo. In Study 1 and its extension study, 39% of TEGSEDI-treated patients with a baseline platelet count below 200 x10^9/L had a nadir platelet count below 75 x 10^9/L, compared to 6% of patients with baseline platelet counts 200 x10^9/L or higher.

Three TEGSEDI-treated patients (3%) had sudden severe thrombocytopenia (platelet count below 25 x 10^9/L), which can have potentially fatal bleeding complications, including spontaneous intracranial or intrapulmonary hemorrhage. One patient in a clinical trial experienced a fatal intracranial hemorrhage.

In clinical trials, all 3 patients with severe thrombocytopenia had treatment-emergent antiplatelet IgG antibodies detected shortly before or at the time of the severe thrombocytopenia. In 2 patients, platelet clumping caused uninterpretable platelet measurements that delayed the diagnosis and treatment of severe thrombocytopenia. Platelet clumping can be caused by a reaction between antiplatelet antibodies and ethylenediaminetetraacetic acid (EDTA) [see Warnings and Precautions (5.8)].

Monitoring and Dosing

Patients who are not able to adhere to the recommended laboratory monitoring or to the related treatment recommendations must not receive TEGSEDI. Do not initiate TEGSEDI in patients with a platelet count below 100 x 10^9/L. Follow recommended monitoring and treatment recommendations for platelet count [see Dosage and Administration (2.4)]. If a patient develops signs or symptoms of thrombocytopenia, obtain a platelet count as soon as possible, and hold TEGSEDI dosing unless the platelet count is confirmed to be acceptable. Recheck the platelet count as soon as possible if a platelet measurement is uninterpretable (e.g., clumped sample) [see Warnings and Precautions (5.8)]. Hold TEGSEDI dosing until an acceptable platelet count is confirmed with an interpretable blood sample.

Concomitant Medications with Platelet Effects

When considering use of TEGSEDI concomitantly with antiplatelet drugs or anticoagulants, be aware of the risk of potential bleeding from thrombocytopenia with TEGSEDI, and consider discontinuation of these drugs in patients with a platelet count less than 50 x 10^9/L [see Drug Interactions (7.1)].

Symptoms of Thrombocytopenia

Symptoms of thrombocytopenia can include unusual or prolonged bleeding (e.g., petechiae, easy bruising, hematoma, subconjunctival bleeding, gingival bleeding, epistaxis, hemoptysis, irregular or heavier than normal menstrual bleeding, hematemesis, hematuria, hematochezia, melena), neck stiffness or atypical severe headache. Patients and caregivers should be instructed to be vigilant for symptoms of thrombocytopenia and seek immediate medical help if they have concerns.

Severe Thrombocytopenia: Treatment with Glucocorticoids

Glucocorticoid therapy is strongly recommended in patients with a platelet count below 50 x 10^9/L, and in patients with suspected immune-mediated thrombocytopenia. Avoid using TEGSEDI in patients for whom glucocorticoid treatment is not advised.

5.2 Glomerulonephritis and Renal Toxicity

TEGSEDI can cause glomerulonephritis that may result in dialysis-dependent renal failure. In Study 1 [see Clinical studies (14)], glomerulonephritis occurred in three (3%) TEGSEDI-treated patients vs. no patient on placebo. In these patients, stopping TEGSEDI alone was not sufficient to resolve manifestations of glomerulonephritis, and treatment with an immunosuppressive medication was necessary. One patient did not receive immunosuppressive treatment and remained dialysis-dependent. If glomerulonephritis is suspected, pursue prompt diagnosis and initiate immunosuppressive treatment as soon as possible.

Cases of glomerulonephritis were accompanied by nephrotic syndrome. Possible complications of nephrotic syndrome can include edema, hypercoagulability with venous or arterial thrombosis, and increased susceptibility to infection. TEGSEDI-treated patients who develop glomerulonephritis will require monitoring and treatment for nephrotic syndrome and its manifestations.

Accumulation of antisense oligonucleotides in proximal tubule cells of the kidney, sometimes leading to increased tubular proteinuria, has been described in nonclinical studies. Urine protein to creatinine ratio (UPCR) greater than 5 times the upper limit of normal occurred in 15% of TEGSEDI-treated patients, compared to 8% of patients on placebo. Increase from baseline in serum creatinine greater than 0.5 mg/dL occurred in 11% of TEGSEDI-treated patients, compared to 2% of patients on placebo.

Follow recommended monitoring and treatment recommendations for renal parameters [see Dosage and Administration (2.4)] . TEGSEDI should generally not be initiated in patients with a UPCR of 1000 mg/g or greater. If acute glomerulonephritis is confirmed, TEGSEDI should be permanently discontinued [see Contraindications (4)].

Use caution with nephrotoxic drugs and other drugs that may impair renal function. Because immunosuppressive treatment is necessary for the treatment of glomerulonephritis, avoid using TEGSEDI in patients for whom immunosuppressive treatment is not advised.

5.3 TEGSEDI REMS Program

TEGSEDI is available only through a restricted program under a Risk Evaluation and Mitigation Strategy (REMS) called the TEGSEDI REMS Program, because of risks of serious bleeding caused by severe thrombocytopenia and because of glomerulonephritis [see Warnings and Precautions (5.1, 5.2)].

Important requirements of the TEGSEDI Prescribing Program include:

- Prescribers must be certified within the program by enrolling and completing training.
- Patients must enroll in the program and comply with ongoing monitoring requirements [see Warnings and Precautions (5.1) and Dosage and Administration (2.4)]. Pharmacies must be certified with the program and must only dispense to patients who are authorized to receive TEGSEDI.

Further information, including a list of qualified pharmacies/distributors, is available at www.TEGSEDIREMS.com or 1-844-483-4736.

5.4 Stroke and Cervicocephalic Arterial Dissection

TEGSEDI may cause stroke and cervicocephalic arterial dissection. In clinical studies, 1 of 161 (0.6%) TEGSEDI-treated patients experienced carotid artery dissection and stroke. These events occurred within 2 days of the first TEGSEDI dose, a time when the patient also had symptoms of cytokine release (e.g., nausea, vomiting, muscular pain and weakness) and a high sensitivity C-reactive protein level greater than 100 mg/L.

Educate patients on the symptoms of stroke and central nervous system arterial dissection. Instruct patients to seek help as soon as possible if symptoms of stroke or arterial dissection occur.

5.5 Inflammatory and Immune Effects

Inflammatory and immune changes are an effect of some antisense oligonucleotide drugs, including TEGSEDI. In clinical studies, serious inflammatory and immune adverse reactions occurred in TEGSEDI-treated patients, including immune thrombocytopenia and glomerulonephritis, as well as a single case of antineutrophil cytoplasmic autoantibody (ANCA)-positive systemic vasculitis [see Warnings and Precautions (5.2) and (5.3)].

Neurologic Serious Adverse Reactions

In clinical studies, neurologic serious adverse reactions consistent with inflammatory and immune effects occurred in TEGSEDI-treated patients, in addition to stroke and carotid artery dissection [see Warnings and Precautions (5.5)]. Two months after the first TEGSEDI dose, one patient developed a change in gait that progressed over 6 months to paraparesis, in the absence of radiologic evidence of spinal cord compression. Another patient developed progressive lumbar pain, weight loss, headache, vomiting, and impaired speech 7 months after starting TEGSEDI. Cerebrospinal fluid analysis findings included elevated protein, a lymphocyte-predominant pleocytosis, and testing that was negative for infection. The patient recovered after empiric therapy (high-dose steroids, antibiotics) and resumed TEGSEDI without recurrence of symptoms.

5.6 Liver Injury

The liver is a site of accumulation of antisense oligonucleotides. In clinical studies, 8% of TEGSEDI-treated patients had an increased alanine aminotransferase (ALT) at least 3 times the upper limit of normal (ULN), compared to 3% of patients on placebo; 3% of TEGSEDI-treated patients had an ALT at least 8 times the ULN, compared to no patient on placebo. One clinical study patient experienced an increased ALT more than 30 times the ULN. After a course of corticosteroids and discontinuation of TEGSEDI, the patient’s ALT returned to normal levels. Some patients had resolution of the liver laboratory abnormalities with continued use of TEGSEDI.

In clinical studies, demonstrated or possible cases of immune-mediated biliary disease occurred in TEGSEDI-treated patients. There was a single case of autoimmune hepatitis with primary biliary cirrhosis in a patient with a family history of primary biliary cirrhosis, as well as a single case of biliary obstruction of unclear etiology.

Monitor alanine aminotransferase (ALT), aspartate aminotransferase (AST), and total bilirubin at baseline and monthly during treatment with TEGSEDI. If a patient develops clinical signs or symptoms suggestive of hepatic dysfunction (e.g., unexplained nausea, vomiting, abdominal pain, fatigue, anorexia, or jaundice and/or dark urine), promptly measure serum transaminases and total bilirubin and interrupt treatment with TEGSEDI, as appropriate.

If a patient is suspected to have developed liver injury induced by TEGSEDI treatment, TEGSEDI should be discontinued.

Liver Transplant Rejection

In a clinical study, cases of liver transplant rejection were reported 2-4 months after starting TEGSEDI in patients whose liver allografts had previously been clinically stable (for over 10 years) prior to starting TEGSEDI. In these cases, the patients clinically improved and transaminase levels normalized after glucocorticoid administration and cessation of TEGSEDI.

In patients with a history of liver transplant, monitor ALT, AST, and total bilirubin monthly. Discontinue TEGSEDI in patients who develop signs of liver transplant rejection.

5.7 Hypersensitivity Reactions/Antibody Formation

TEGSEDI can cause hypersensitivity reactions. In clinical studies, 6 of 161 (4%) TEGSEDI-treated patients stopped treatment because of a hypersensitivity reaction. Antibodies to TEGSEDI were present when the reactions occurred. These reactions generally occurred within 2 hours of administration of TEGSEDI and included headache, chest pain, hypertension, chills, flushing, dysphagia, palmar erythema, eosinophilia, involuntary choreaform movements, arthralgia, myalgia, and flu-like symptoms.

If a hypersensitivity reaction occurs, discontinue administration of TEGSEDI, and initiate appropriate therapy. Do not use in patients who have a history of hypersensitivity reaction to TEGSEDI.

5.8 Uninterpretable Platelet Counts: Reaction between Antiplatelet Antibodies and ethylenediaminetetra-acetic acid (EDTA)

In Study 1 [see Clinical Studies (14)], 23% of TEGSEDI-treated patients had at least 1 uninterpretable platelet count caused by platelet clumping, compared to 13% of patients on placebo. In 2 cases of severe thrombocytopenia with platelet count below 25 x 10^9/L, one of which resulted in death, clumped platelet samples caused a delay in diagnosis and treatment. Both subjects had tested positive for treatment-emergent anti-platelet IgG antibodies detected shortly before, or at the time of the severe reduction in platelet count.

Although platelet clumping can have a variety of causes (e.g., incompletely mixed or inadequately anticoagulated samples), platelet clumping can be caused by a reaction between antiplatelet antibodies and ethylenediaminetetra-acetic acid (EDTA). In Study 1, 7 of the 9 (78%) TEGSEDI-treated patients with treatment-emergent positive antiplatelet antibody testing had at least 1 clumped platelet sample.

If there is suspicion of EDTA-mediated platelet clumping, perform a repeat platelet count using a different anticoagulant (e.g., sodium citrate, heparin) in the blood collection tube. Recheck the platelet count as soon as possible if a platelet measurement is uninterpretable. Hold TEGSEDI dosing until an acceptable platelet count is confirmed with an interpretable blood sample.

5.9 Reduced Serum Vitamin A Levels and Recommended Supplementation

TEGSEDI treatment leads to a decrease in serum vitamin A levels. Supplementation at the recommended daily allowance of vitamin A is advised for patients taking TEGSEDI. Higher doses than the recommended daily allowance of vitamin A should not be given to try to achieve normal serum vitamin A levels during treatment with TEGSEDI, as serum vitamin A levels do not reflect the total vitamin A in the body.

Patients should be referred to an ophthalmologist if they develop ocular symptoms suggestive of vitamin A deficiency (e.g., night blindness).

6 ADVERSE REACTIONS

The following serious adverse reactions are discussed in greater detail in other sections of the labeling:

- Thrombocytopenia [see Warnings and Precautions (5.1)]
- Glomerulonephritis and Renal Toxicity [see Warnings and Precautions (5.2)]
- Stroke and Cervicocephalic Arterial Dissection [see Warnings and Precautions (5.4)]
- Inflammatory and Immune Effects [see Warnings and Precautions (5.5)]
- Liver Injury [see Warnings and Precautions (5.6)]
- Hypersensitivity [see Warnings and Precautions (5.7)]
- Reducted Serum Vitamin A Levels and Recommended Supplementation [see Warnings and Precautions (5.9)]

6.1 Clinical Trials Experience

Because clinical trials are conducted under widely varying conditions, adverse reaction rates observed in the clinical trials of TEGSEDI cannot be directly compared to rates in clinical trials of other drugs and may not reflect the rates observed in practice.

A total of 112 adult patients with polyneuropathy caused by hereditary transthyretin-mediated amyloidosis (hATTR) received TEGSEDI in Study 1 and 60 patients received placebo. The, mean age of the study patients was 59 years (27 to 78 years of age). Of the TEGSEDI-treated patients, 69% were male and 94% were Caucasian, with a mean exposure of 385 days, and median exposure of 449 days. Baseline disease characteristics were largely similar in TEGSEDI-treated patients and patients in the placebo control group. Sixty-seven percent of patients were in Stage 1 of the disease at baseline, and 33% in Stage 2. Fifty-two percent of patients had Val30Met mutations in the TTR gene, with the remaining 48% comprised of 26 different other point mutations.

Table 2 presents common adverse reactions that occurred in at least 5% of TEGSEDI-treated patients and that occurred at least 5% more frequently or two times more frequently than on placebo.

The most common adverse reactions that occurred in at least 20% of TEGSEDI-treated patients and more frequently than on placebo were injection site reactions, nausea, headache, fatigue, thrombocytopenia, and fever. Serious adverse reactions were more frequent in TEGSEDI-treated patients (32%) than in patients on placebo (21%). The most common adverse reactions leading to discontinuation were thrombocytopenia and cachexia.

Table 2: Adverse Reactions Reported in At Least 5% TEGSEDI-Treated Patients and that Occurred At Least 5% More Frequently or At Least Two Times More Frequently than Placebo Patients (Study 1)
 | TEGSEDI (N=112) % | Placebo (N=60) %
Injection site reactionsa | 49 | 10
Nausea | 31 | 12
Headache | 26 | 12
Fatigue | 25 | 20
Thrombocytopenia | 24 | 2
Fever | 20 | 8
Peripheral edema | 19 | 10
Chills | 18 | 3
Anemia | 17 | 3
Vomiting | 15 | 5
Myalgia | 15 | 10
Decreased renal function | 14 | 5
Arrhythmiab | 13 | 5
Arthralgia | 13 | 8
Pre-syncope or syncope | 13 | 5
Decreased appetite | 10 | 0
Paresthesia | 10 | 3
Dyspnea | 9 | 3
Elevated liver function test | 9 | 3
Orthostasis | 8 | 2
Influenza-like illness | 8 | 3
Contusion | 7 | 2
Bacterial infectionc | 7 | 3
Eosinophilia | 5 | 0
Dry mouth | 5 | 2
a Includes bruising, erythema, hematoma, hemorrhage, induration, inflammation, mass, edema, pain, pruritus, rash, swelling, and urticaria.
b Includes arrhythmia, atrial fibrillation, atrial flutter, bradyarrhythmia, bradycardia, extrasystoles, sinus arrhythmia, sinus bradycardia, supraventricular extrasystoles, tachycardia, and ventricular extrasystoles.
c Includes bacteremia, cellulitis staphylococcal, clostridium difficile infection, conjunctivitis bacterial, cystitis Escherichia, Helicobacter gastritis, Helicobacter infection, Staphylococcal infection.

6.2 Immunogenicity

The detection of antibody formation is highly dependent on the sensitivity and specificity of the assay. In addition, the observed incidence of antibody (including neutralizing antibody) positivity in an assay may be influenced by several factors, including assay methodology, sample handling, timing of sample collection, concomitant medications, and underlying disease. For these reasons, comparison of the incidence of antibodies to TEGSEDI in the studies described below with the incidence of antibodies in other studies or to other products may be misleading.

In Study 1, 30% of TEGSEDI-treated patients tested positive for anti-drug antibodies (ADA) following 65 weeks of treatment [see Warnings and Precautions (5.7, 5.8)]. However, the assay measured only IgG isotypes and the existence of other isotypes may be possible. In many cases adverse reactions occurred in patients with ADA, although the available data are too limited to make definitive conclusions about the relationship.

7 DRUG INTERACTIONS

7.1 Antiplatelet Drugs or Anticoagulant Medications

Because of the risk of thrombocytopenia, caution should be used when using antiplatelet drugs (e.g., adenosine, clopidogrel, prasugrel, ticagrelor, or ticlopidine), including non-prescription products that affect platelets (e.g., aspirin, nonsteroidal anti-inflammatory drugs), or anticoagulants (e.g., heparin, warfarin), concomitantly with TEGSEDI [see Warnings and Precautions (5.1)].

7.2 Nephrotoxic Drugs

Because of the risk of glomerulonephritis and renal toxicity, caution should be used when using nephrotoxic drugs and other drugs that may impair renal function concomitantly with TEGSEDI [see Warnings and Precautions (5.2)].

8 USE IN SPECIFIC POPULATIONS

8.1 Pregnancy

Pregnancy Exposure Registry

There is a pregnancy exposure registry that monitors pregnancy outcomes in women exposed to TEGSEDI during pregnancy. Health care providers are encouraged to register patients and pregnant women are encouraged to register themselves by calling: 1-877-465-7510, emailing: tegsedipregnancy@ubc.com, or visiting online at: www.tegsedipregnancystudy.com.

Risk Summary

There are no data on the developmental risk associated with the use of TEGSEDI in pregnant women. TEGSEDI treatment leads to a decrease in serum vitamin A levels, and vitamin A supplementation is advised for patients taking TEGSEDI. Vitamin A is essential for normal embryofetal development; however, excessive levels of Vitamin A are associated with adverse developmental effects. The effects on the fetus of a reduction in maternal serum TTR caused by TEGSEDI and of vitamin A supplementation are unknown [see Clinical Pharmacology (12.2), Warnings and Precautions (5.9)].

In animal studies, subcutaneous administration of inotersen to pregnant rabbits resulted in premature delivery and reduced fetal body weight at the highest dose tested, which was associated with maternal toxicity. No adverse developmental effects were observed when inotersen or a pharmacologically-active surrogate was administered to pregnant mice.

In the U.S. general population, the estimated background risk of major birth defects and miscarriage in clinically recognized pregnancies is 2-4% and 15-20%, respectively. The background risk of major birth defects and miscarriage for the indicated population is unknown.

Data

Animal Data

Subcutaneous administration of inotersen (0, 3, 15, or 25 mg/kg) or a rodent-specific surrogate (15 mg/kg) to male and female mice every other day prior to and during mating and continuing in females throughout the period of organogenesis produced no adverse effects on embryofetal development.

Subcutaneous administration of inotersen (0, 2.5, 5, or 15 mg/kg) to pregnant rabbits every other day throughout the period of organogenesis resulted in premature delivery and reduced fetal body weight at the highest dose tested, which was associated with maternal toxicity (reduced body weight and food consumption).

Subcutaneous administration of inotersen (0, 2.9, 11.4, or 22.9 mg/kg) or a rodent-specific surrogate (11.4 mg/kg) to mice every other day throughout pregnancy and lactation produced no adverse effects on pre- or postnatal development.

8.2 Lactation

Risk Summary

There is no information regarding the presence of TEGSEDI in human milk, the effects on the breast-fed infant, or the effects on milk production. A study in lactating mice has shown excretion of inotersen in milk. The development and health benefits of breastfeeding should be considered along with the mother’s clinical need for TEGSEDI and any potential adverse effects on the breastfed infant from TEGSEDI or from the underlying maternal condition.

8.4 Pediatric Use

Safety and effectiveness in pediatric patients have not been established.

8.5 Geriatric Use

Clinical studies of TEGSEDI included 69 patients (45%) aged 65 and over. No differences in pharmacokinetics or effectiveness were observed between these patients and younger patients. Patients 65 years and older may be at increased risk of certain adverse reactions, such as congestive heart failure, chills, myalgia, and extremity pain.

8.6 Renal Impairment

No dose adjustment is necessary in patients with mild to moderate renal impairment (estimated glomerular filtration rate [eGFR] ≥30 to <90 mL/min/1.73 m^2) [see Clinical Pharmacology (12.3)]. TEGSEDI has not been studied in patients with severe renal impairment or end-stage renal disease.

8.7 Hepatic Impairment

No dose adjustment is necessary in patients with mild hepatic impairment [see Clinical Pharmacology (12.3)]. TEGSEDI has not been studied in patients with other degrees of hepatic impairment.

11 DESCRIPTION

Inotersen is an antisense oligonucleotide (ASO) inhibitor of human transthyretin (TTR) protein synthesis.

TEGSEDI contains inotersen sodium as the active ingredient. Inotersen sodium is a white to pale yellow solid and it is freely soluble in water and in phosphate buffer (pH 7.5 to 8.5). The chemical name of inotersen sodium is DNA, d(P-thio)([2'-O-(2-methoxyethyl)]m^5rU-[2'-O-(2-methoxyethyl)]m^5rC-[2'-O-(2-methoxyethyl)]m^5rU-[2'-O-(2-methoxyethyl)]m^5rU-[2'-O-(2-methoxyethyl)]rG-G-T-T-A-m^5C-A-T-G-A-A-[2'-O-(2-methoxyethyl)]rA-[2'-O-(2-methoxyethyl)]m^5rU-[2'-O-(2-methoxyethyl)]m^5rC-[2'-O-(2-methoxyethyl)]m^5rC-[2'-O-(2-methoxyethyl)]m^5rC). The molecular formula of inotersen sodium is C230H299N69 Na19O121P19S19 and the molecular weight is 7600.73 Da. It has the following structural formula:

The molecular formula of inotersen free base is C230H318N69O121P19S19 and its molecular weight is 7183.08.

TEGSEDI is a sterile, preservative-free, aqueous solution for subcutaneous injection. It is supplied in a prefilled syringe (PFS). Each PFS contains 1.5 mL of solution containing 284 mg inotersen (equivalent to 300 mg inotersen sodium salt) TEGSEDI is formulated in Water for Injection and may include hydrochloric acid and/or sodium hydroxide for pH adjustment to 7.5-8.5.

12 CLINICAL PHARMACOLOGY

12.1 Mechanism of Action

Inotersen is an antisense oligonucleotide that causes degradation of mutant and wild-type TTR mRNA through binding to the TTR mRNA, which results in a reduction of serum TTR protein and TTR protein deposits in tissues.

12.2 Pharmacodynamics

The pharmacodynamic effects of TEGSEDI were evaluated in hATTR amyloidosis patients treated with 284 mg TEGSEDI via subcutaneous injection once weekly.

With repeat dosing, the mean percent decreases from baseline in serum TTR from Week 13 to Week 65 of treatment ranged from 68% to 74% (median range: 75% to 79%). Similar TTR reductions were observed regardless of TTR mutation, sex, age, or race.

Serum TTR is a carrier of retinol binding protein, which is involved in the transport of vitamin A in the blood. Mean reductions in serum retinol binding of 71%, and serum vitamin A of 63%, were observed at Week 65 [see Warnings and Precautions (5.6)].

Cardiac Electrophysiology

Formal QTc studies have not been conducted with TEGSEDI. The potential for QTc prolongation with inotersen was evaluated in a randomized, placebo-controlled trial in healthy volunteers. No large changes in the mean QTc interval (>20 ms) were detected in the trial.

In the 66-week controlled efficacy trial, 5.4% of TEGSEDI-treated patients had evidence of QRS prolongation on their electrocardiograms (ECGs) to greater than 160 msec and greater than 25% above baseline, compared to and in 1.7% of patients on placebo.

12.3 Pharmacokinetics

Following subcutaneous administration, systemic exposure to inotersen increased in a dose-proportional manner over the range of 150-400 mg of inotersen sodium salt. At the recommended TEGSEDI dosing regimen of 284 mg every week, steady state is reached after approximately 3 months. The estimated geometric mean (90% confidence interval) steady state peak concentrations (Cmax), trough concentrations (Ctrough), and area under the curve (AUCτ) were 6.39 (5.65, 7.20) µg/mL, 0.034 (0.031, 0.038) µg/mL, and 90 (82.4, 97.4) µg·h/mL, respectively. Plasma Cmax and AUC do not exhibit accumulation at steady state.

Absorption

Following subcutaneous administration, TEGSEDI is absorbed rapidly into systemic circulation in a dose-dependent fashion, with the median time to maximum plasma concentrations (Cmax) of 2 to 4 hours.

Distribution

TEGSEDI is highly bound to human plasma proteins (>94%) and the fraction bound is independent of drug concentration. Based on animal studies (mouse, rat and monkey), TEGSEDI rapidly distributes broadly to tissues, with the highest concentrations observed in the kidney and liver. TEGSEDI does not cross the blood-brain barrier. The apparent volume of distribution of TEGSEDI at steady-state (mean and 90% confidence interval) is 293 (268, 320) L in patients with hATTR.

Elimination

The terminal elimination half-life (mean and 90% confidence interval) for TEGSEDI is 32.3 (29.4, 35.5) days. Inotersen is mainly cleared through metabolism, and the total body clearance (mean and 90% confidence interval) is 3.18 (3.08, 3.29) L/h.

Metabolism

Inotersen is metabolized by nucleases to nucleotides of various lengths.

Excretion

Less than 1% of the administered dose of inotersen is excreted unchanged into urine within 24 hours.

Specific Populations

Age, race, and sex had no impact on the steady state pharmacokinetics of inotersen or TTR reduction. Population pharmacokinetic and pharmacodynamic analyses indicated no impact of mild or moderate renal impairment (eGFR ≥30 to <90 mL/min/1.73 m^2) or mild hepatic impairment (bilirubin less than or equal to 1.5 x ULN and/or AST less than 1.9 x ULN) on inotersen exposure or TTR reduction. TEGSEDI has not been studied in patients with severe renal impairment, end-stage renal disease, moderate or severe hepatic impairment, or in patients with prior liver transplant.

Drug Interaction Studies

No formal clinical drug interaction studies have been performed. TEGSEDI is not a substrate or inhibitor/inducer of major CYP enzymes or a substrate or inhibitor of major transporters. In a population pharmacokinetic analysis, concomitant use of diuretics, antithrombotic, and analgesics did not impact the pharmacokinetic parameters of inotersen. TEGSEDI is not expected to cause drug-drug interactions or to be affected by inhibitors or inducers of cytochrome P450 enzymes.

13 NONCLINICAL TOXICOLOGY

13.1 Carcinogenesis, Mutagenesis, Impairment of Fertility

Carcinogenesis

In a 26-week carcinogenicity study in transgenic (TgRasH2) mice, weekly subcutaneous administration of inotersen (0, 10, 30, or 80 mg/kg) or a rodent-specific (pharmacologically active) surrogate (30 mg/kg) did not result in an increase in tumors.

In a 94-week carcinogenicity study in rats, weekly subcutaneous administration of inotersen (0, 0.5, 2, or 6 mg/kg) resulted in an increase in tumors at or near the injection site in males at all but the lowest dose (0.5 mg/kg) tested. Subcutaneous malignant pleomorphic fibrosarcoma was increased at the mid and high doses and combined subcutaneous malignant pleomorphic fibrosarcoma and monomorphic fibrosarcoma were increased at the high dose. These tumors are considered a response to chronic tissue irritation and inflammation caused by repeated subcutaneous injection.

Mutagenesis

Inotersen was negative for genotoxicity in in vitro (bacterial mutagenicity, chromosomal aberration in Chinese hamster lung) and in vivo (mouse bone marrow micronucleus) assays.

Impairment of Fertility

Subcutaneous administration of inotersen (0, 3, 15, or 25 mg/kg) or a rodent-specific surrogate (15 mg/kg) to male and female mice every other day prior to and during mating and continuing in females throughout the period of organogenesis produced no adverse effects on fertility.

14 CLINICAL STUDIES

The efficacy of TEGSEDI was demonstrated in a randomized, double-blind, placebo-controlled, multicenter clinical trial in adult patients with polyneuropathy caused by hATTR amyloidosis (Study 1; NCT 01737398). Patients were randomized in a 2:1 ratio to receive either TEGSEDI (284 mg inotersen) (N=113) or placebo (N=60), respectively, as a subcutaneous injection administered once per week for 65 weeks (3 doses were administered during the first week of treatment). Seventy seven percent of TEGSEDI-treated patients and 87% of patients on placebo completed 66 weeks of the assigned treatment.

The co-primary efficacy endpoints were the change from baseline to Week 66 in the modified Neuropathy Impairment Scale+7 (mNIS+7) composite score and the Norfolk Quality of Life-Diabetic Neuropathy (QoL-DN) total score

The mNIS+7 is an objective assessment of neuropathy, and comprises the NIS and Modified +7 composite scores. In the version of the mNIS+7 used in the trial, the NIS objectively measures deficits in cranial nerve function, muscle strength, reflexes, and sensations, and the Modified +7 assesses heart rate response to deep breathing, postural blood pressure, quantitative sensory testing (touch-pressure and heat-pain), and peripheral nerve electrophysiology. The maximum possible score was 346.32 points, with higher scores representing a greater severity of disease.

The clinical meaningfulness of effects on the mNIS+7 was assessed by the change from baseline to Week 66 in Norfolk Quality of Life-Diabetic Neuropathy (QoL-DN) total score. The Norfolk QoL-DN scale is a patient-reported assessment that evaluates the subjective experience of neuropathy in the following domains: physical functioning/large fiber neuropathy, activities of daily living, symptoms, small fiber neuropathy, and autonomic neuropathy. The version of the Norfolk QoL-DN that was used in the trial had a maximum possible total score of 136 points, with higher scores representing greater impairment.

The changes from baseline to Week 66 on both the mNIS+7 and the Norfolk QoL-DN significantly favored TEGSEDI (Table 3, Figures 1 and 3). The distributions of changes in mNIS+7 and Norfolk QoL-DN scores from baseline to Week 66 by percent of patients are shown in Figure 2 and Figure 4, respectively.

Table 3: Clinical Efficacy Results from Study 1
Endpoint | Baseline |  | Change from Baseline to Week 66 (LS Mean) |  | TEGSEDI – placebo Treatment Difference LS Mean (95% CI) | p- value
Endpoint | TEGSEDI | Placebo | TEGSEDI | Placebo | TEGSEDI – placebo Treatment Difference LS Mean (95% CI) | p- value
Primarya
mNIS+7b, c | 80.2 | 75.3 | 5.8 | 25.5 | -19.7 [-26.4, -13.0] | <0.001
Norfolk QOL- DNb, d | 48.7 | 48.7 | 1.0 | 12.7 | -11.7 [-18.3, -5.1] | <0.001
CI, confidence interval; LS, least squares; mNIS, modified Neuropathy Impairment Score; QoL-DN, Quality of Life – Diabetic Neuropathy
a All endpoints analyzed using the mixed-effect model repeated measures (MMRM) method.
b A lower value indicates less impairment/fewer symptoms.
cThe primary analysis population for the mNIS+7 analysis included N=95 TEGSEDI patients and N=56 placebo patients
dThe primary analysis population for the Norfolk QOL-DN analysis included N=94 TEGSEDI patients and N=57 placebo patients

Figure 1: Change from Baseline in mNIS+7

Figure 2: Histogram of mNIS+7 Change from Baseline at Week 66

Figure 3: Change from Baseline in Norfolk QoL-DN Score

Figure 4: Histogram of Norfolk QoL-DN Change from Baseline at Week 66

Patients receiving TEGSEDI experienced similar improvements relative to placebo in mNIS+7 and Norfolk QoL-DN score across all subgroups including age, sex, race, region, NIS score, Val30Met mutation status, and disease stage.

16 HOW SUPPLIED/STORAGE AND HANDLING

TEGSEDI is a clear, colorless to pale yellow solution supplied in a single-dose, prefilled syringe with a SSD. Each prefilled syringe of TEGSEDI is filled to deliver 1.5 mL of solution containing 284 mg of inotersen (equivalent to 300 mg inotersen sodium salt).

TEGSEDI is available in cartons containing 1 or 4 prefilled syringes supplied in individual trays.

- Pack of 1 prefilled syringe: NDC 72126-007-03
- Pack of 4 prefilled syringes: NDC 72126-007-01

The individual tray of 1 syringe is NDC 72126-007-02.

Pharmacy

Store refrigerated at 2°C to 8°C (36°F to 46°F) in the original container and protect from direct light. Do not freeze.

For Patients/Caregivers

Store refrigerated at 2°C to 8°C (36°F to 46°F) in the original container. Do not freeze. TEGSEDI can be kept at room temperature (up to 30°C [86°F]) in the original container for up to 6 weeks; if not used within the 6 weeks, discard TEGSEDI.

Remove from refrigerated storage (2°C to 8°C [36°F to 46°F]) at least 30 minutes before use. [TEGSEDI] prefilled syringe should be allowed to reach room temperature prior to injection.

Avoid exposure to temperatures above 30°C (86°F).

17 PATIENT COUNSELING INFORMATION

Advise the patient and caregiver to read the FDA-approved patient labeling (Medication Guide and Instructions for Use).

Thrombocytopenia

Inform patients that TEGSEDI can cause reductions in platelet count that may result in thrombocytopenia. Instruct patients to notify a healthcare provider immediately if they show symptoms of thrombocytopenia (e.g., unusual or prolonged bleeding, neck stiffness, or atypical severe headache). Advise patients of the importance of monitoring during treatment with TEGSEDI [see Warnings and Precautions (5.1)]. Also instruct patients to notify their healthcare provider of all medications, including over-the-counter, that they are taking [see Drug Interactions (7.1)].

Glomerulonephritis and Renal Toxicity

Inform patients that glomerulonephritis has occurred in patients treated with TEGSEDI. Advise patients of the importance of monitoring of urine protein to creatinine ratio (UPCR during treatment with TEGSEDI) [see Warnings and Precautions (5.2)].

TEGSEDI REMS Program

TEGSEDI is available only through a restricted program called the TEGSEDI REMS Program [see Warnings and Precautions (5.3)]. Inform the patient of the following notable requirements:

- Patients must enroll in the program and comply with ongoing monitoring requirements.
- TEGSEDI is available only from certified pharmacies participating in the program. Therefore, provide patients with the telephone number and website for information on how to obtain the product.

Stroke and Cervicocephalic Arterial Dissection

Educate patient on symptoms of stroke and central nervous system arterial dissection and instruct them to seek help as soon as possible if symptoms of these or other serious neurologic adverse reactions occur [see Warnings and Precautions (5.4)].

Liver Injury

Instruct patients to inform a healthcare professional of symptoms suggestive of hepatic dysfunction that occur after administration of TEGSEDI [see Warnings and Precautions (5.6)].

Hypersensitivity

Instruct patients to inform a healthcare professional of symptoms suggestive of hypersensitivity that occur after administration of TEGSEDI [see Warnings and Precautions (5.7)].

Recommended Vitamin A Supplementation

Inform patients that TEGSEDI treatment leads to a decrease in vitamin A levels measured in the serum. Instruct patients to take the recommended daily allowance of vitamin A. Advise patients to contact their healthcare provider if they experience ocular symptoms suggestive of vitamin A deficiency (e.g., night blindness) and refer them to an ophthalmologist if they develop these symptoms [see Warnings and Precautions (5.9)].

Administration Instructions

Train patients and caregivers on proper subcutaneous administration technique and how to use the single-dose prefilled syringe. Instruct patients and/or caregivers to read and follow the Instructions for Use each time they use TEGSEDI.

Pregnancy

Instruct patients that if they are pregnant or plan to become pregnant while taking TEGSEDI they should inform their healthcare provider. Advise female patients of childbearing potential of the potential risk to the fetus. Encourage patients to enroll in the TEGSEDI Pregnancy Registry if they become pregnant while taking TEGSEDI [see Use in Specific Populations (8.1)].

For more information about TEGSEDI, go to www.TEGSEDIREMS.com or call 1-844-483-4736

Distributed by:
Sobi, Inc.
Waltham, MA 02451

TEGSEDI is a registered trademark of Akcea Therapeutics, Inc.

MEDICATION GUIDE

TEGSEDI (Teg-SED-ee)
(inotersen)
injection, for subcutaneous use

What is the most important information I should know about TEGSEDI?

TEGSEDI can cause serious side effects, including:

- low platelet counts (thrombocytopenia). TEGSEDI may cause the number of platelets in your blood to be reduced reduced at any time during treatment. This is a common side effect of TEGSEDI. When your platelet count is too low, your body cannot form clots. You could have serious bleeding that could lead to death. Call your healthcare provider immediately if you have:
  - unusual bruising or a rash of tiny reddish-purple spots, often on the lower legs
  - bleeding from skin cuts that does not stop or oozes
  - bleeding from your gums or nose
  - blood in your urine or stools
  - bleeding into the whites of your eyes
  - sudden severe headaches or neck stiffness
  - vomiting or coughing up blood
  - abnormal or heavy periods (menstrual bleeding)

- kidney inflammation (glomerulonephritis).Your kidneys may stop working properly. Glomerulonephritis can lead to severe kidney damage and kidney failure that needs dialysis. Call your healthcare provider immediately if you have:
  - puffiness or swelling in your face, feet or hands
  - new onset or worsening shortness of breath and coughing
  - blood in your urine or brown urine
  - foamy urine (proteinuria)
  - passed less urine than usual

Your healthcare provider will do laboratory tests to check your platelet count and kidneys before you start TEGSEDI and while you are using it. Your healthcare provider should also do laboratory tests for 8 weeks after you stop TEGSEDI. It is important that you make sure you get these laboratory tests done.

- Because of the risk of serious bleeding caused by low platelet counts and because of the risk of kidney problems, TEGSEDI is available only through a restricted program called the TEGSEDI Risk Evaluation and Mitigation (REMS) Program.
  - Before you begin using TEGSEDI, you must enroll in the TEGSEDI REMS Program. Talk to your healthcare provider about how to enroll in the TEGSEDI REMS Program.
  - You must agree to get your laboratory testing done while you are in the TEGSEDI REMS Program.
  - You can only get TEGSEDI from a certified pharmacy that participates in the TEGSEDI REMS Program. Your healthcare provider can give you information on how to find a certified pharmacy.
  - For more information, including a list of certified pharmacies go to www.TEGSEDIREMS.com or call 1-844-483-4736.

What is TEGSEDI?

TEGSEDI is a medicine used to treat the polyneuropathy of hereditary transthyretin-mediated (hATTR) amyloidosis in adults. It is not known if TEGSEDI is safe and effective in children.

Do not use TEGSEDI if you have:

- a platelet count that is low.
- had kidney inflammation (glomerulonephritis) caused by TEGSEDI.
- had an allergic reaction to inotersen or any of the ingredients in TEGSEDI. See the end of this Medication Guide for a complete list of ingredients in TEGSEDI.

Before you start using TEGSEDI, tell your healthcare provider about all your medical conditions, including if you:

- have or had bleeding problems
- have or had kidney problems
- have received a liver transplant
- are pregnant or plan to become pregnant. It is not known if TEGSEDI can harm your unborn baby.
  - There is a registry for women who become pregnant during treatment with TEGSEDI. If you become pregnant while taking TEGSEDI, talk to your healthcare provider about registering with the TEGSEDI Pregnancy Exposure Registry. The purpose of this registry is to collect information about your health and your baby’s health. You can get more information about this registry by calling: 1-877-465-7510, emailing: tegsedipregnancy@ubc.com, or visiting online at: www.tegsedipregnancystudy.com.

- are breastfeeding or plan to breastfeed. It is not known if TEGSEDI can pass into your breast milk or harm your baby. Talk with your healthcare provider about the best way to feed your baby while you are using TEGSEDI.

Tell your healthcare provider about all the medicines you take, including prescription and over-the-counter medicines, vitamins, and herbal supplements.

Especially tell your healthcare provider if you take:

- Vitamin A or beta-carotene supplements. Your healthcare provider should tell you to take vitamin A, but only take the amount they tell you to take.
- blood thinners (anticoagulants) or medicines that affect blood clotting.
- Ask your healthcare provider or pharmacist if you are not sure if you take any of these medicines. Know the medicines you take. Keep a list of them to show your healthcare provider or pharmacist when you get a new medicine.

How should I use TEGSEDI?

- Read the detailed Instructions for Use that come with your TEGSEDI.
- Your healthcare provider will show you or your caregiver how to inject TEGSEDI the first time.
- If you or your caregiver have any questions, ask your healthcare provider.
- TEGSEDI is injected under your skin (subcutaneously) in your stomach area (abdomen), or the front of your upper legs (thighs) by you or a caregiver. A caregiver may also give you an injection of TEGSEDI in the outer area of your upper arm.
- Do not inject into the same site each time.
- Do not inject into the 2-inch area around the belly-button (naval).
- Do not inject where the skin is bruised, tender, red, or hard.
- Do not inject into areas with scars or tattoos.
- Do not inject through clothing.
- Follow your healthcare provider’s instructions on when to inject TEGSEDI.
- TEGSEDI should be injected 1 time each week on the same day.
- If you miss a dose, take the missed dose as soon as possible, unless your next scheduled dose is within 2 days. If your next scheduled dose is within 2 days, skip the missed dose and take your next scheduled dose on the scheduled day.

What are possible side effects of TEGSEDI?

TEGSEDI may cause serious side effects, including:

- See “What is the most important information I should know about TEGSEDI?”
- stroke. TEGSEDI may cause a stroke. One person taking TEGSEDI had a stroke, which occurred within 2 days after the first dose.Signs or symptoms of stroke may include:
  - sudden numbness or weakness especially on one side of the body
  - severe headache or neck pain
  - confusion
  - problems with vision, speech, or balance
  - droopy eyelids

Get emergency help immediately if you have symptoms of stroke.

- inflammatory and immune system problems.Some people taking TEGSEDI had serious inflammatory and immune system problems. Symptoms of inflammatory and immune system problems included unexpected change in walking, weakness and spasms in legs, back pain, weight loss, headache, vomiting, and problems with speech.
- liver effects. TEGSEDI may cause liver problems. Your healthcare provider should do laboratory tests to check your liver before you start TEGSEDI and while you are using it. Tell your healthcare provider if you have symptoms that your liver may not be working right, which could include unexpected nausea and vomiting, stomach pain, being not hungry, yellowing of the skin, or having dark urine.
- allergic reactions. TEGSEDI may cause serious allergic reactions. These allergic reactions often occur within 2 hours after injecting TEGSEDI. Get emergency help immediately if you have any symptoms of an allergic reaction including:

- joint pain
- chills
- redness on palms of hands
- muscle pain

- chest pain
- flushing
- tremor or jerking movements
- flu-like symptoms

- high blood pressure
- difficulty swallowing

- eye problems (low vitamin A levels). Treatment with TEGSEDI will lower the Vitamin A levels in your blood. Your healthcare provider should tell you to take Vitamin A supplements while using TEGSEDI. Your healthcare provider will tell you how much to take. Call your healthcare provider if you get eye problems, such as having difficulty seeing at night or in low lit areas (night blindness). Your healthcare provider should send you to see an eye doctor (ophthalmologist).

The most common side effects of TEGSEDI include: injection site reactions (such as redness or pain at the injection site), nausea, headache, tiredness, low platelet counts (thrombocytopenia), and fever.

These are not all the possible side effects of TEGSEDI.

Call your doctor for medical advice about side effects. You may report side effects to FDA at 1-800-FDA-1088.

How should I store TEGSEDI?

- Store TEGSEDI in the refrigerator between 36°F to 46°F (2°C to 8°C) in the original container.
- Do not freeze.
- TEGSEDI prefilled syringes can also be kept at room temperature that is no higher than 86°F (30°C) in the original container for up to 6 weeks.
- Do not let TEGSEDI reach temperatures above 86°F (30°C).
- If you do not use TEGSEDI kept at room temperature within 6 weeks, throw it away.
- Protect from light.

Keep TEGSEDI and all medicines out of the reach of children.

General information about the safe and effective use of TEGSEDI

Medicines are sometimes prescribed for purposes other than those listed in a Medication Guide. Do not use TEGSEDI for a condition for which it has not been prescribed. Do not give TEGSEDI to other people, even if they have the same symptoms that you have. It may harm them. You can ask your pharmacist or healthcare provider for information about TEGSEDI that was written for health professionals.

What are the ingredients in TEGSEDI? Active ingredients: inotersen

Inactive ingredients: purified water (water for injection), hydrochloric acid and or sodium hydroxide for pH adjustment

Distributed by Sobi, Inc, Waltham, MA
TEGSEDI is registered in the US Patent and Trademark Office© 2017
For more information about TEGSEDI, contact Sobi, Inc., at 1-844-483-4736 or go to www.TEGSEDIREMS.com.

This Medication Guide has been approved by the U.S. Food and Drug Administration.

Issued: 01/2024

INSTRUCTIONS FOR USE

TEGSEDI (Teg-SED-ee)
(inotersen) injection
for subcutaneous use
Instructions For Use

Introduction

Before using your TEGSEDI prefilled syringe, your healthcare provider should show you or your caregiver how to use it the right way. If you or your caregiver have any questions, ask your healthcare provider.

Read this Instructions for Use before you start using your TEGSEDI prefilled syringe and each time you get a refill. There may be new information. This information does not take the place of talking to your healthcare provider about your medical condition or your treatment.

Guide to parts

Important information

- Store TEGSEDI in the refrigerator between 36°F to 46°F (2°C to 8°C) in the original container.
- Do not freeze.
- TEGSEDI prefilled syringes can also be kept at room temperature that is no higher than 86°F (30°C) in the original container for up to 6 weeks.
- Do not let TEGSEDI reach temperatures above 86°F (30°C).
- If you do not use TEGSEDI kept at room temperature within the 6 weeks, throw it away.
- Protect from light.
- Keep TEGSEDI and all medicines out of reach of children.

Each TEGSEDI prefilled syringe contains 1 dose of TEGSEDI and is for 1-time use only.

Warnings

- Do not remove needle cap until you have reached Step 6 of the Injection phase of these instructions and are ready to inject TEGSEDI
- Do not share your syringe with another person or re-use your syringe
- Do not use if dropped onto a hard surface or damaged
- Do not shake or freeze the prefilled syringe
- Do not use if the expiration date on the side of the syringe body has passed

If any of the above happens, throw away the prefilled syringe in a puncture-resistant (sharps) container and use a new prefilled syringe.

Preparation

Step 1. Gather supplies

- 1 TEGSEDI prefilled syringe from the refrigerator
- 1 Alcohol wipe (not supplied)
- 1 Gauze pad or cotton ball (not supplied)
- 1 Puncture-resistant (sharps) container (not supplied)

Do not perform the injection without all the supplies listed.

Step 2. Prepare to use your TEGSEDI prefilled syringe

- Remove the TEGSEDI tray from the carton and check the expiration date. Do not use if the expiration date has passed.
- Let TEGSEDI warm up at room temperature 68°F to 77°F (20°C to 25°C) for 30 minutes before giving the injection.
  - Do not warm the syringe in any other way. For example, do not warm in a microwave or hot water, or near other heat sources.
- Remove the syringe from the tray by holding onto the syringe body.
  - Do not move the plunger
  - Do not remove the syringe from the tray by holding onto the needle cap or plunger.

Step 3. Check medicine in the syringe

- Look in the inspection area to check that the TEGSEDI solution is clear and colorless or pale yellow in color. It is normal to see air bubbles in the solution. You do not need to do anything about it.
- Do not use if the solution looks cloudy, discolored, or has particles. Throw the prefilled syringe away in a puncture resistant (sharps) container, and use a new prefilled syringe.

Step 4. Choose the injection site

- Choose an injection site on your abdomen or the front of your thigh.
- Do not inject into the same site each time.
- Do not inject into the 2 inch area around the belly-button (naval).
- Do not inject where skin is bruised, tender, red, or hard.
- Do not inject into areas of the skin with scars or tattoos.
- Do not inject through clothing.

Step 5. Clean the injection site

- Wash your hands with soap and water.
- Clean the injection site with an alcohol wipe in a circular motion. Let the skin air dry.
- Do not touch the area again before injecting.

Injection

Step 6. Remove the needle cap

- Hold the syringe by the body, with the needle facing away from you.
- Remove needle cap by pulling it straight off. Do not to twist it off.
- You may see a drop of liquid at the end of the needle. This is normal.
- Keep your hands away from the plunger to avoid pushing the plunger before you are ready to inject.

Do not remove the needle cap until right before you inject.

Do not pull the cap off while holding the syringe by the plunger. Always hold by the body of the syringe.

Do not let the needle touch any surface.

Do not remove any air bubbles from the syringe.

Do not put the needle cap back onto the syringe.

Step 7. Insert the needle

- Hold the syringe in 1 hand.
- Hold the skin around at the injection site as your healthcare provider has instructed you. You should either gently pinch the skin at the injection site or give the injection without pinching the skin.
- Slowly insert the entire needle into the chosen injection site at a 90° angle until fully inserted.

Do not hold the syringe by the plunger or push against the plunger to insert the needle.

Step 8. Start the injection

- Slowly and firmly push the plunger all the way down until the medicine is injected. Make sure the needle stays fully inserted in the injection site while you are injecting the medicine.
- It is important to fully push the plunger all the way down.
- Your syringe may make a click sound as you push the plunger down. This is normal. This does not mean that the injection is finished.
- The plunger can feel stiffer towards the end of the injection. You may need to press a little harder on the plunger to make sure you have pushed it as far as it will go.

Do not let go of the plunger.

Step 9. Push the plunger down

- Push firmly on the plunger at the end of the injection. Hold the plunger fully down and wait for 5 seconds. If you let go of the plunger too quickly, you may lose some of the medicine.
- The plunger will start to lift automatically which means that the plunger has been pushed fully down.
- Press down again if the plunger does not start to lift automatically.

Step 10. Complete the injection

- Slowly lift up on the plunger and let the safety spring push the plunger up automatically.
- The needle should now be retracted safely inside the syringe, and the safety mechanism spring visible on the outside of the plunger.
- When the plunger comes to a stop, your injection is complete.
- If the plunger does not rise up automatically when you release the pressure, it means the safety spring did not activate and you should push the plunger again but harder.
- Throw away the cap and syringe into the puncture-resistant (sharps) container right away (See section - “Dispose of the used syringe”).

Do not pull the plunger up by hand. Lift the whole syringe straight up.

Do not try to replace the cap on the retracted needle.

Do not rub the injection site.

Disposal and care

Dispose of the used syringe

- Put the used TEGSEDI prefilled syringe in a FDA-cleared sharps disposal container right away after use. Do not throw away (dispose of) the TEGSEDI prefilled syringe in your household trash.
- If you do not have a FDA-cleared sharps disposal container, you may use a household container that is:

- made of heavy-duty plastic,
- can be closed with a tight-fitting, puncture-resistant lid, without sharps being able to come out,
- upright and stable during use,
- leak-resistant, and
- properly labelled to warn of hazardous waste inside the container.

- When your sharps disposal container is almost full, you will need to follow your community guidelines for the right way to dispose of your sharps disposal container. There may be state or local laws about how you should throw away used needles and syringes. For more information about sharps disposal, and for specific information about safe sharps disposal in the state that you live in, go to the FDA’s website at:

http://www.fda.gov/safesharpsdisposal

This Instructions for Use has been approved by the U.S. Food and Drug Administration

Issued:10/2018